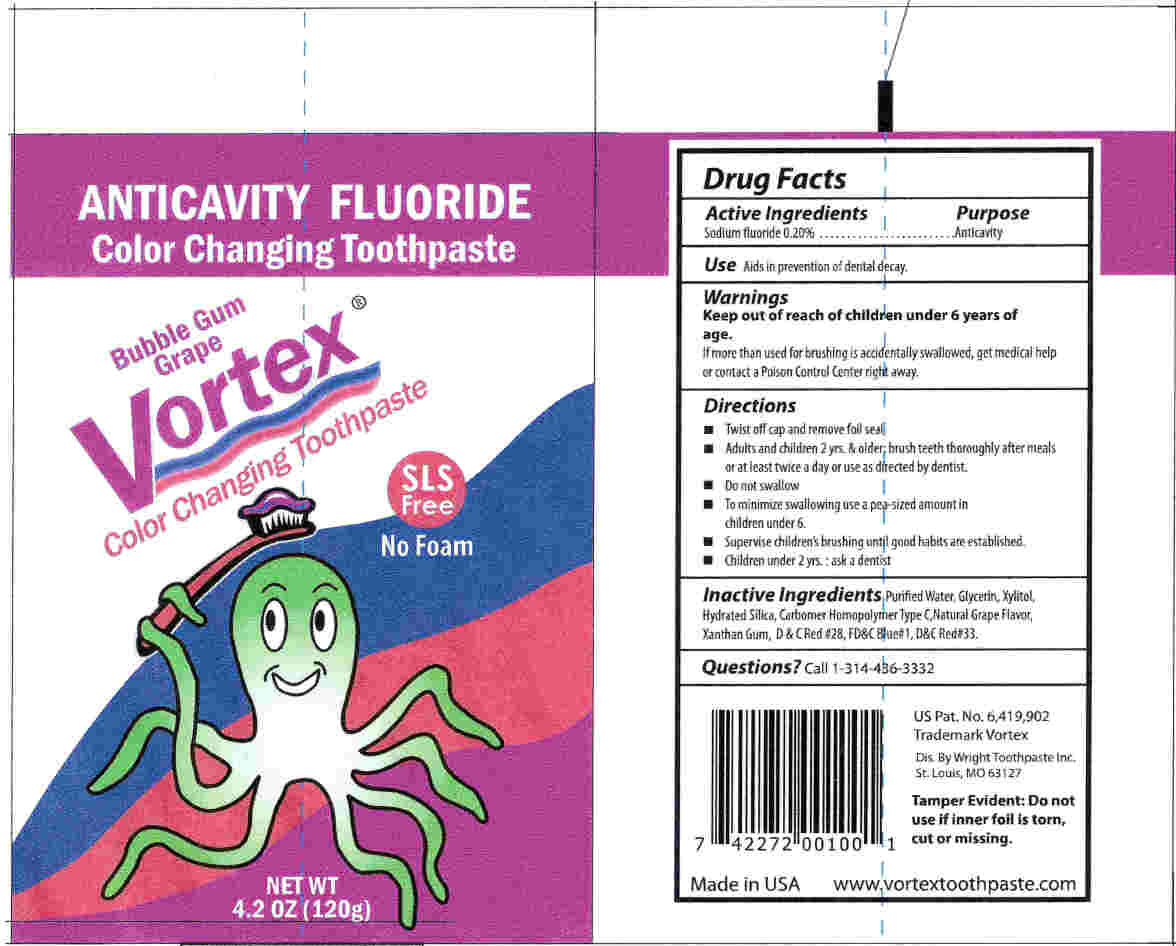 DRUG LABEL: Vortex
NDC: 52316-028 | Form: PASTE, DENTIFRICE
Manufacturer: DSC Laboratories, Div. of DSC Products Inc.
Category: otc | Type: HUMAN OTC DRUG LABEL
Date: 20111206

ACTIVE INGREDIENTS: SODIUM FLUORIDE 2.0 mg/1 g
INACTIVE INGREDIENTS: WATER; GLYCERIN; XYLITOL; HYDRATED SILICA; CARBOMER HOMOPOLYMER TYPE C; XANTHAN GUM; D&C RED NO. 28; FD&C BLUE NO. 1; D&C RED NO. 33

Drug Facts

Active Ingredients

Sodium Fluoride 0.20%

Purpose

Anticavity

Use

Aids in prevention of dental decay.

WARNINGS

Keep out of reach of children under 6 years of age.

If more than used for brushing is accidentally swallowed, get medical help or contact a Poison Control Center right away.

Directions

- Twist off cap and remove foil seal
- Adults and children 2 yrs. and older: brush teeth thoroughly after meals or at least twice a day or use as directed by dentist.
- Do not swallow
- To minimize swallowing use a pea-sized amount in children under 6.
- Supervise children's brushing until good habits are established.
- Children under 2 yrs.: ask a dentist

Inactive Ingredients

Purified water, Glycerin, Xylitol, Hydrated Silica, Carbomer Homopolymer Type C, Natural Grape Flavor, Xanthan Gum, D and C Red #28, FD and C Blue #1, D and C Red #33.

Questions?

Call 1-314-436-3332

VORTEX TOOTHPASTE 120G TUBE

Vortex Anti-Cavity Fluoride Toothpaste

Net Wt. 4.2 oz (120g)

Distributed by: Wright Toothpaste Inc.

St. Louis, MO 63127